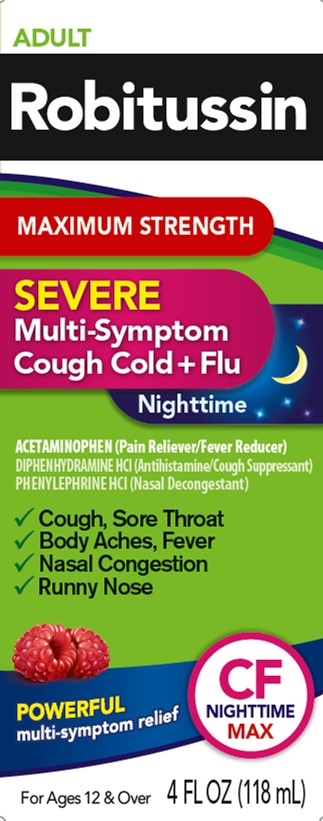 DRUG LABEL: Robitussin Severe Multi-Symptom Cough Cold Flu Nighttime
NDC: 0031-8752 | Form: SOLUTION
Manufacturer: Haleon US Holdings LLC
Category: otc | Type: HUMAN OTC DRUG LABEL
Date: 20240406

ACTIVE INGREDIENTS: ACETAMINOPHEN 650 mg/20 mL; DIPHENHYDRAMINE HYDROCHLORIDE 25 mg/20 mL; PHENYLEPHRINE HYDROCHLORIDE 10 mg/20 mL
INACTIVE INGREDIENTS: ANHYDROUS CITRIC ACID; EDETATE DISODIUM; FD&C RED NO. 40; GLYCERIN; MENTHOL, UNSPECIFIED FORM; POLYETHYLENE GLYCOL, UNSPECIFIED; PROPYL GALLATE; PROPYLENE GLYCOL; WATER; SODIUM BENZOATE; SODIUM CITRATE, UNSPECIFIED FORM; SORBITOL; SUCRALOSE

Drug Facts

Active ingredients (in each 20 mL)

Acetaminophen, USP 650 mg

Diphenhydramine HCl, USP 25 mg

Phenylephrine HCl, USP 10 mg

Purposes

Pain reliever/Fever reducer

Antihistamine/Cough suppressant

Nasal decongestant

Uses

- temporarily relieves these symptoms occurring with a cold or flu, hay fever, or other respiratory allergies:
  - cough due to minor throat and bronchial irritation
  - nasal congestion
  - headache
  - sore throat
  - minor aches and pains
  - runny nose
  - sneezing
  - itchy, watery eyes
  - itching of the nose and throat
- temporarily reduces fever

Warnings

Liver warning:

This product contains acetaminophen. Severe liver damage may occur if you take

- more than 6 doses in any 24-hour period, which is the maximum daily amount
- with other drugs containing acetaminophen
- 3 or more alcoholic drinks every day while using this product

Allergy alert:acetaminophen may cause severe skin reactions. Symptoms may include:

- skin reddening
- blisters
- rash

If a skin reaction occurs, stop use and seek medical help right away.

Sore throat warning

If sore throat is severe, persists for more than 2 days, is accompanied or followed by fever, headache, rash, nausea, or vomiting, consult a doctor promptly.

Do not use

- to sedate a child or to make a child sleepy
- if you are now taking a prescription monoamine oxidase inhibitor (MAOI) (certain drugs for depression, psychiatric, or emotional conditions, or Parkinson's disease), or for 2 weeks after stopping the MAOI drug. If you do not know if your prescription drug contains an MAOI, ask a doctor or pharmacist before taking this product.
- with any other drug containing acetaminophen (prescription or nonprescription). If you are not sure whether a drug contains acetaminophen ask a doctor or pharmacist.
- with any other product containing diphenhydramine, even one used on skin

Ask a doctor before use if you have

- liver disease
- heart disease
- high blood pressure
- thyroid disease
- diabetes
- trouble urinating due to an enlarged prostate gland
- glaucoma
- a breathing problem or chronic cough that lasts or as occurs with smoking, asthma, chronic bronchitis, or emphysema
- cough that occurs with too much phlegm (mucus)

Ask a doctor or pharmacist before use if you are

- taking the blood thinning drug warfarin
- taking any other oral nasal decongestant or stimulant
- taking any other pain reliever/fever reducer
- taking sedatives or tranquilizers

When using this product

- do not use more than directed
- marked drowsiness may occur
- avoid alcoholic drinks
- alcohol, sedatives, and tranquilizers may increase drowsiness
- be careful when driving a motor vehicle or operating machinery
- excitability may occur, especially in children

Stop use and ask a doctor if

- you get nervous, dizzy, or sleepless
- pain, cough, or nasal congestion gets worse or lasts more than 7 days
- fever gets worse or lasts more than 3 days
- redness or swelling is present
- new symptoms occur
- cough comes back or occurs with rash or headache that lasts. These could be signs of a serious condition.

PREGNANCY OR BREAST FEEDING

If pregnant or breast-feeding,ask a health professional before use.

Keep out of reach of children.In case of overdose, get medical help or contact a Poison Control Center right away. Prompt medical attention is critical for adults as well as for children, even if you do not notice any signs or symptoms.

Directions

- do not take more than 6 doses in any 24-hour period
- do not exceed recommended dosage. Taking more than the recommended dose (overdose) may cause serious liver damage.
- measure only with dosing cup provided
- keep dosing cup with product
- mL = milliliter
- this adult product is not intended for use in children under 12 years of age

age | dose
adults and children 12 years and over | 20 mL every 4 hours
children under 12 years | do not use

Other information

- each 20 mL contains:sodium 12 mg
- store at 20-25°C (68-77°F)

Inactive ingredients

anhydrous citric acid, artificial flavor, edetate disodium, FD&C red no. 40, glycerin, menthol, polyethylene glycol, propyl gallate, propylene glycol, purified water, sodium benzoate, sodium citrate, sorbitol solution, sucralose

Questions or comments?

call weekdays from 9 AM to 5 PM EST at 1-800-245-1040

Additional Information

Packaged with Tamper-Evident bottle cap.

Do Not Use if breakable ring is separated or missing.

Distributed by: GSK Consumer Healthcare, Warren, NJ 07059

For most recent product information, visit www.robitussin.com

Trademarks owned or licensed by GSK.

©2022 GSK or licensor

Made in Canada

Principal Display Panel

ADULT

Robitussin

MAXIMUM STRENGTH

SEVERE

Multi-Symptom

Cough Cold + Flu

Nighttime

ACETAMINOPHEN (Pain Reliever/Fever Reducer)

DIPHENHYDRAMINE HCI (Antihistamine/Cough Suppressant)

PHENYLEPHRINE HCI (Nasal Decongestant)

Cough, Sore Throat

Body Aches, Fever

Nasal Congestion

Runny Nose

POWERFUL

Multi-symptom relief

CF NIGHTTIME MAX

For Ages 12 & Over

4 FL OZ (118 mL)

62000000077079 Front Carton